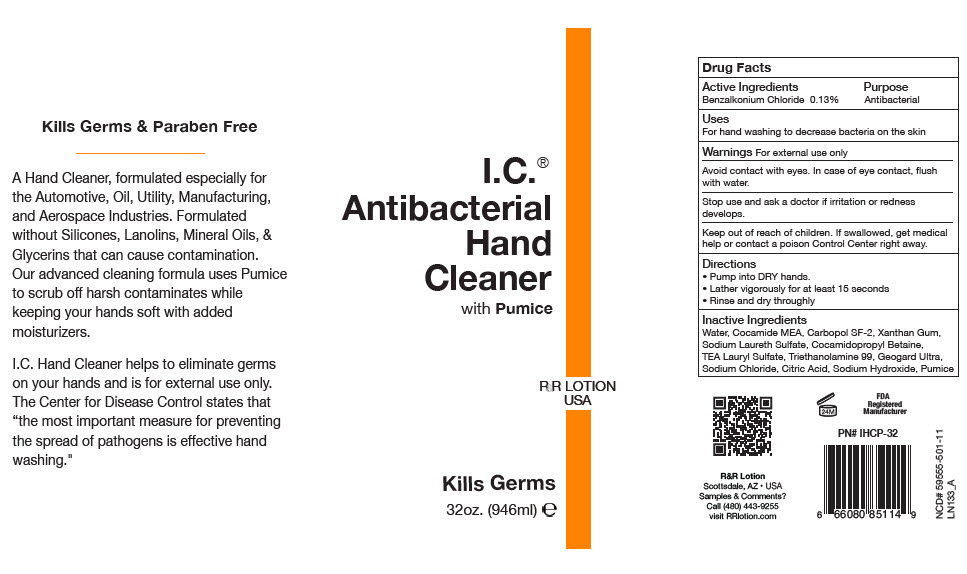 DRUG LABEL: I.C. Antibacterial Hand Cleaner with Pumice
NDC: 59555-501 | Form: SOAP
Manufacturer: R & R Lotion, Inc
Category: otc | Type: HUMAN OTC DRUG LABEL
Date: 20211007

ACTIVE INGREDIENTS: Benzalkonium Chloride 1.3 mg/1 mL
INACTIVE INGREDIENTS: water; Triethanolamine Lauryl Sulfate; SODIUM LAURETH-3 SULFATE; Cocamidopropyl Betaine; COCO MONOETHANOLAMIDE; SODIUM CHLORIDE; GLUCONOLACTONE; SODIUM BENZOATE; CITRIC ACID MONOHYDRATE; SODIUM HYDROXIDE; ACRYLATES CROSSPOLYMER-6; TROLAMINE; Xanthan Gum

I.C.® Antibacterial Hand Cleaner with Pumice

Drug Facts

Active Ingredients

Benzalkonium Chloride 0.13%

Purpose

Antibacterial

Uses

For hand washing to decrease bacteria on the skin

Warnings

For external use only

Avoid contact with eyes. In case of eye contact, flush with water.

Stop use and ask a doctor if irritation or redness develops.

Keep out of reach of children. If swallowed, get medical help or contact a poison Control Center right away.

Directions

- Pump into DRY hands.
- Lather vigorously for at least 15 seconds
- Rinse and dry throughly

Inactive Ingredients

Water, Cocamide MEA, Carbopol SF-2, Xanthan Gum, Sodium Laureth Sulfate, Cocamidopropyl Betaine, TEA Lauryl Sulfate, Triethanolamine 99, Geogard Ultra, Sodium Chloride, Citric Acid, Sodium Hydroxide, Pumice

Samples & Comments?

Call (480) 443-9255

PRINCIPAL DISPLAY PANEL - 946 ml Bottle Label

I.C.®
Antibacterial
Hand
Cleaner
with Pumice

R&R LOTION
USA

Kills Germs

32oz. (946ml) ℮